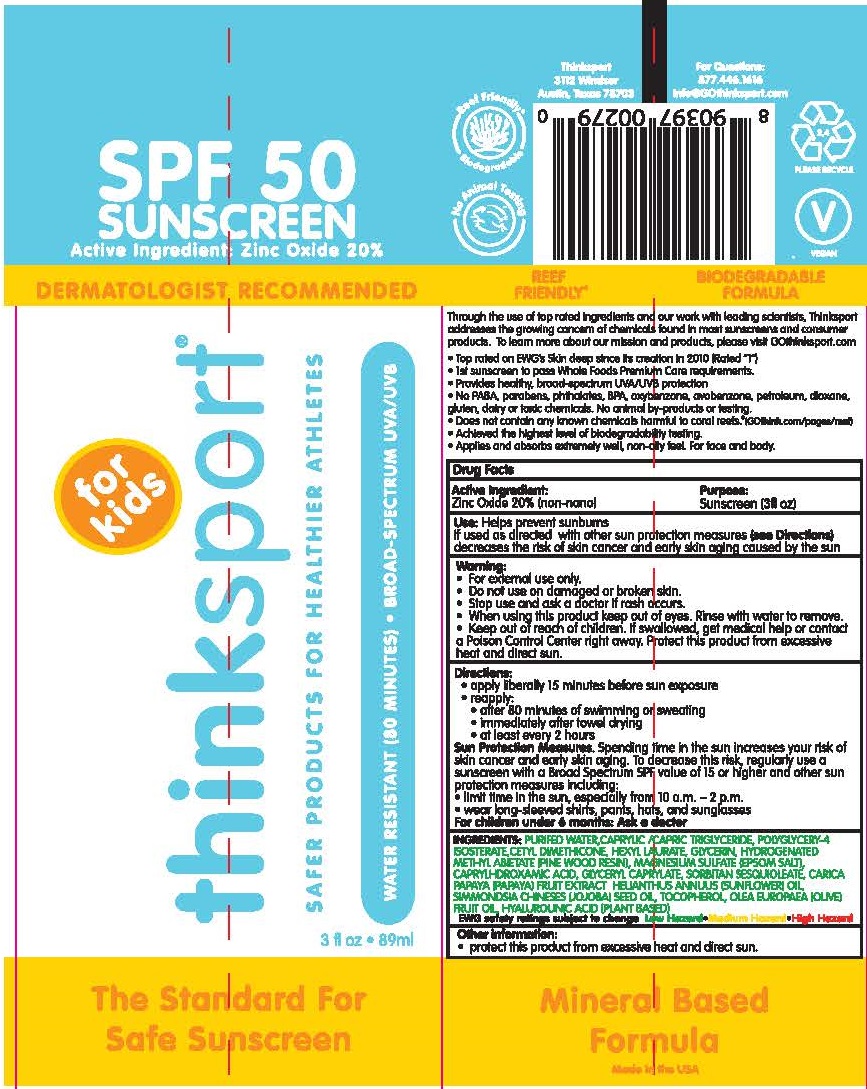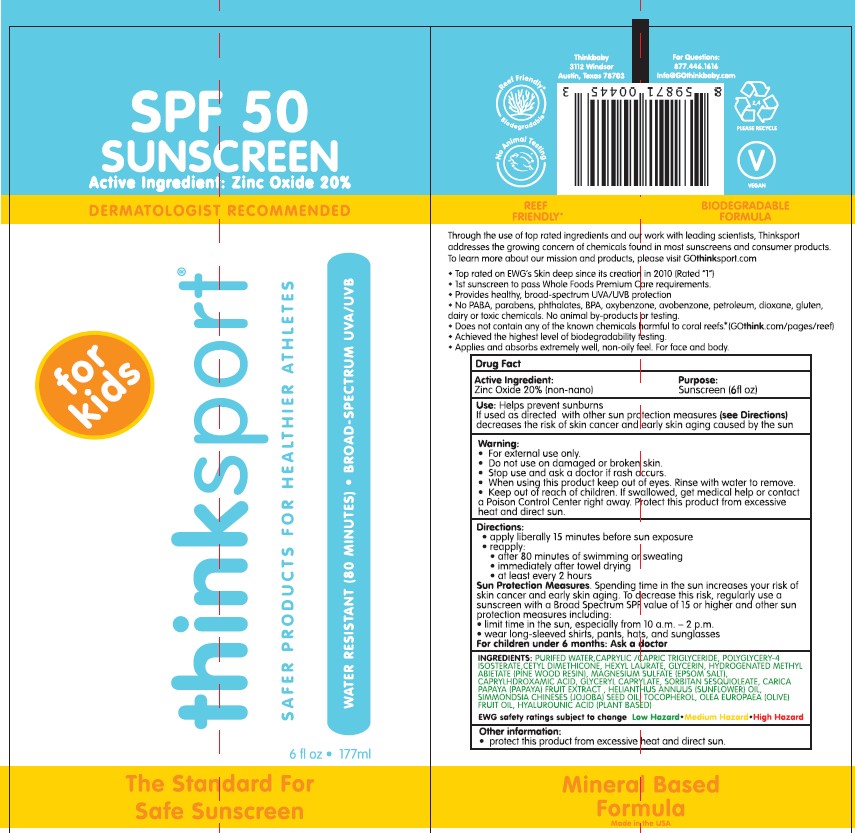 DRUG LABEL: THINKSPORT 
NDC: 60781-1002 | Form: LOTION
Manufacturer: thinkOperations,LLC
Category: otc | Type: HUMAN OTC DRUG LABEL
Date: 20200908

ACTIVE INGREDIENTS: ZINC OXIDE 200 mg/1 mL
INACTIVE INGREDIENTS: POLYGLYCERYL-4 ISOSTEARATE; CAPRYLHYDROXAMIC ACID; HEXYL LAURATE; GLYCERYL MONOCAPRYLATE; TRICAPRILIN; WATER; TRICAPRIN; SORBITAN SESQUIOLEATE; GLYCERIN; CETYL DIMETHICONE 25; HYDROGENATED METHYL ABIETATE; MAGNESIUM SULFATE, UNSPECIFIED FORM; SUNFLOWER OIL; JOJOBA OIL; TOCOPHEROL; OLIVE OIL; HYALURONIC ACID; PAPAYA

THINKSPORT®
Kids sunscreen SPF 50

Drug Facts

Active Ingredient

Zinc Oxide 20% (non-nano)

Purpose

Sunscreen

Use

Helps prevent sunburns

If used as directed with other sun protection measures (see Directions) decreases the risk of skin cancer and early skin aging caused by the sun

Warning

- For external use only.

- Do not use on damaged or broken skin.

- Stop use and ask a doctor if rash occurs.

- When using this product keep out of eyes. Rinse with water to remove.

- Keep out of reach of children. If swallowed, get medical help or contact a Poison Control Center right away. Protect this product from excessive heat and direct sun.

Directions

- apply liberally 15 minutes before sun exposure
- reapply:
  - after 80 minutes of swimming or sweating
  - immediately after towel drying
  - at least every 2 hours

Sun Protection Measures. Spending time in the sun increases your risk of skin cancer and early skin aging. To decrease this risk, regularly use a sunscreen with a Broad Spectrum SPF value of 15 or higher and other sun protection measures including:

- limit time in the sun, especially from 10 a.m. – 2 p.m.
- wear long-sleeved shirts, pants, hats, and sunglasses

For children under 6 months: Ask a doctor

Inactive Ingredients

Water (purified), caprylic/capric triglycerides, polyglycery-4 isosterate, cetyl dimethicone, hexyl laurate, glycerin, hydrogenated methyl abietate (pine wood resin), magnesium sulfate (epsom salt), caprylhdroxamic acid, glyceryl caprylate, sorbitan sesquioleate, carica papaya (papaya) fruit extract, helianthus annuus (sunflower) oil, simmondsia chineses (jojoba) seed oil, tocopherol, olea europaea (olive) fruit oil, hyalurounic acid (plant based)

Other information

- protect this product from excessive heat and direct sun.

Questions

877.446.1616

PRINCIPAL DISPLAY PANEL - 89 ml Tube Label

SPF 50
SUNSCREEN
Active Ingredient: Zinc Oxide 20%

DERMATOLOGIST RECOMMENDED

for
kids

thinksport®

SAFER PRODUCTS FOR HEALTHIER ATHLETES

WATER RESISTANT (80 MINUTES) • BROAD-SPECTRUM UVA/UVB

Thinksport

3112 Windsor

Austin, Texas 78703